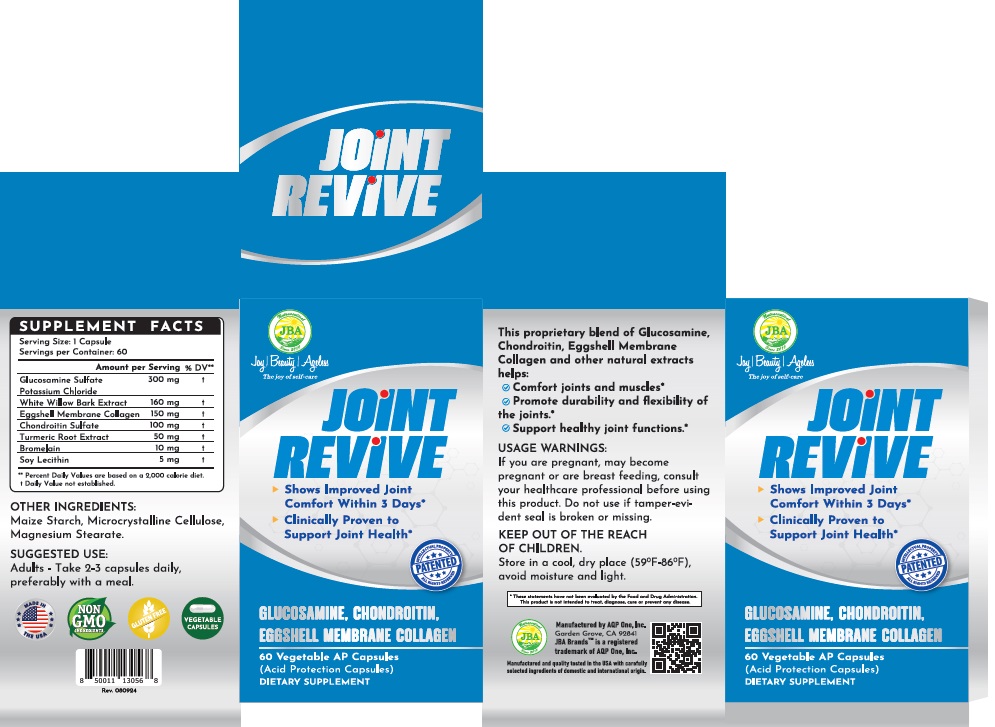 DRUG LABEL: JBA Joint Revive
NDC: 13411-856 | Form: CAPSULE
Manufacturer: Advanced Pharmaceutical Services, Inc. Dba Affordable Quality Pharmaceuticals
Category: otc | Type: HUMAN OTC DRUG LABEL
Date: 20250331

ACTIVE INGREDIENTS: SALIX ALBA BARK 160 mg/1 1; GLUCOSAMINE SULFATE POTASSIUM CHLORIDE 300 mg/1 1; EGG SHELL MEMBRANE 150 mg/1 1; CHONDROITIN SULFATE (BOVINE) 100 mg/1 1; TURMERIC 50 mg/1 1; STEM BROMELAIN 10 mg/1 1; SOYBEAN LECITHIN 5 mg/1 1
INACTIVE INGREDIENTS: STARCH, CORN; MICROCRYSTALLINE CELLULOSE; MAGNESIUM STEARATE

Identity

Dietary supplement

Direction

Take 2-3 capsules daily, preferably with a meal.

Safe handling warning

- Shows Improved Joint Comfort Within 3 Days*
- Clinically Proven to Support Joint Health*

This proprietary blend of Glucosamine, Chondroitin, Eggshell Membrane Collagen and other natural extracts helps:

- Comfort joints and muscles*
- Promote durability and flexibility of the joints*
- Support healthy joint functions*

* These statements have not been evaluated by the Food & Drug Administration. This product is not intended to diagnose, treat, cure, or prevent any disease.

PRECAUTIONS

If you are pregnant, may become pregnant or are breast feeding, consult your healthcare professional before using this product. Do not use if tamper-evident seal is broken or missing.

Keep Out of The Reach of Children.

Store in a cool, dry place (59°F-86°F), avoid moisture and light.

WARNINGS

Other Ingredients

Maize starch, Microcrystalline Cellulose, Magnesium Stearate.